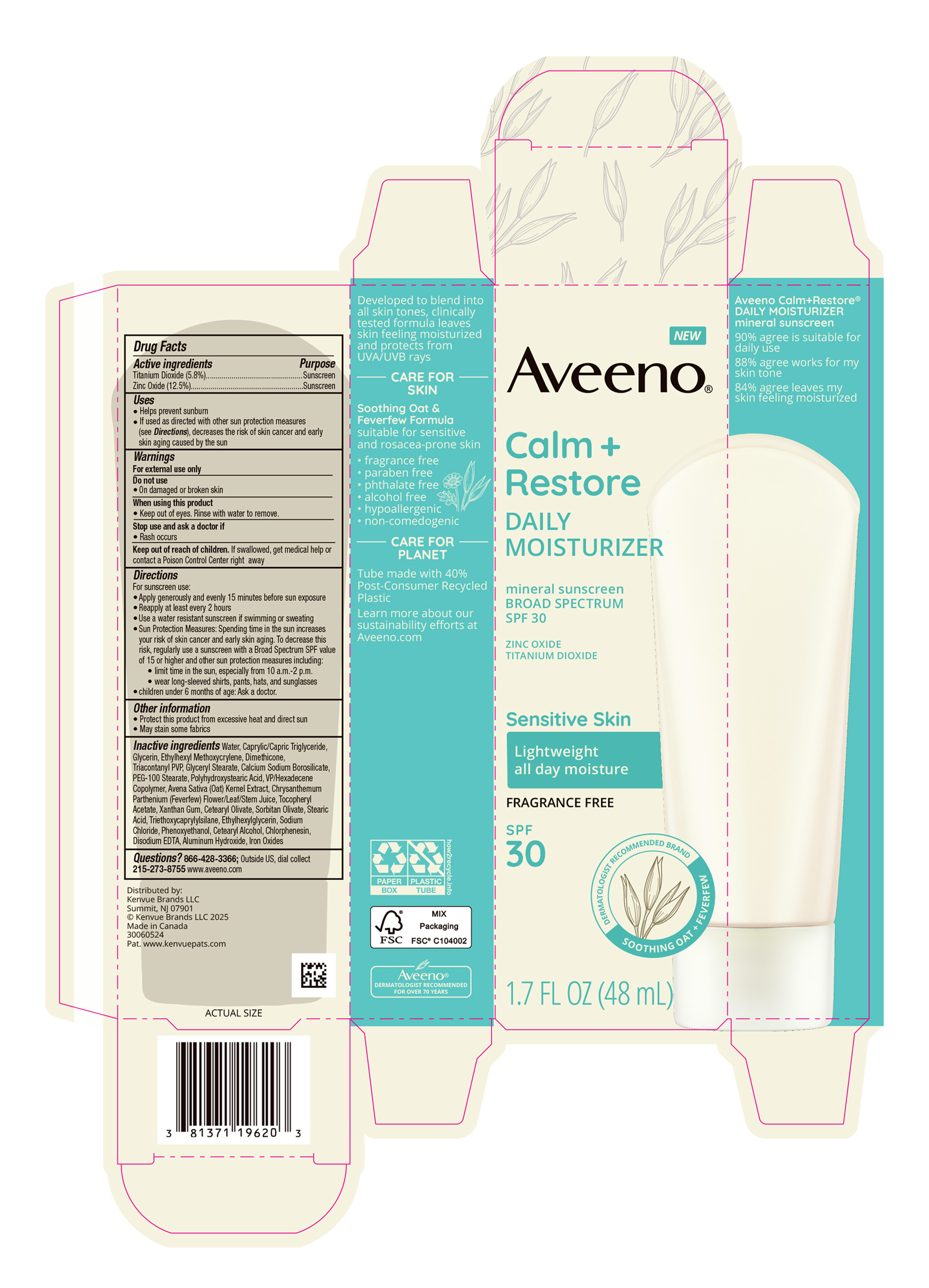 DRUG LABEL: Aveeno Calm Plus Restore Daily Moisturizer Mineral Sunscreen Broad Spectrum SPF 30
NDC: 69968-0813 | Form: LOTION
Manufacturer: Kenvue Brands LLC
Category: otc | Type: HUMAN OTC DRUG LABEL
Date: 20250604

ACTIVE INGREDIENTS: TITANIUM DIOXIDE 58 mg/1 mL; ZINC OXIDE 125 mg/1 mL
INACTIVE INGREDIENTS: SORBITAN OLIVATE; FERROUS OXIDE; CETOSTEARYL ALCOHOL; MEDIUM-CHAIN TRIGLYCERIDES; VINYLPYRROLIDONE/HEXADECENE COPOLYMER; TANACETUM PARTHENIUM; CETEARYL OLIVATE; TRIETHOXYCAPRYLYLSILANE; SODIUM CHLORIDE; CHLORPHENESIN; TRIACONTANYL PVP (WP-660); OAT; WATER; ETHYLHEXYL METHOXYCRYLENE; ALUMINUM HYDROXIDE; GLYCERYL MONOSTEARATE; PEG-100 STEARATE; XANTHAN GUM; STEARIC ACID; ETHYLHEXYLGLYCERIN; EDETATE DISODIUM ANHYDROUS; .ALPHA.-TOCOPHEROL ACETATE; DIMETHICONE; PHENOXYETHANOL; GLYCERIN; POLYHYDROXYSTEARIC ACID (2300 MW)

Aveeno Protect Plus Soothe Face Mineral Sunscreen SPF 30

Drug Facts

ACTIVE INGREDIENT

Titanium Dioxide

Zinc Oxide

Active ingredients | Purpose
Titanium Dioxide (5.8%) | Sunscreen
Zinc Oxide (12.5%) | Sunscreen

Uses

- Helps prevent sunburn
- If used as directed with other sun protection measures (see Directions), decreases the risk of skin cancer and early skin aging caused by the sun

Warnings

For external use only

DO NOT USE

- On damaged or broken skin

When using this product

▪ Keep out of eyes. Rinse with water to remove.

Stop use and ask a doctor if

▪ Rash occurs

Keep out of reach of children. If swallowed, get medical help or contact a Poison Control Center right away

Directions

For sunscreen use:

▪ Apply generously and evenly 15 minutes before sun exposure

▪ Reapply at least every 2 hours

▪ Use a water resistant sunscreen if swimming or sweating

▪ Sun Protection Measures: Spending time in the sun increases your risk of skin cancer and

early skin aging. To decrease this risk, regularly use a sunscreen with a Broad Spectrum

SPF value of 15 or higher and other sun protection measures including:

▪ limit time in the sun, especially from 10 a.m.–2 p.m.

▪ wear long-sleeved shirts, pants, hats, and sunglasses

▪ children under 6 months of age: Ask a doctor.

Other information

- Protect this product from excessive heat and direct sun
- May stain some fabrics

Inactive ingredients

Water, Caprylic/Capric Triglyceride, Glycerin, Ethylhexyl,Methoxycrylene, Dimethicone, Triacontanyl PVP, Glyceryl Stearate, Calcium Sodium Borosilicate, PEG-100 Stearate, Polyhydroxystearic Acid, VP/Hexadecene Copolymer, Avena Sativa (Oat) Kernel Extract, Chrysanthemum Parthenium (Feverfew) Flower/Leaf/Stem Juice, Tocopheryl Acetate, Xanthan Gum, Cetearyl Olivate, Sorbitan Olivate, Stearic Acid,Triethoxycaprylylsilane, Ethylhexylglycerin, Sodium Chloride, Phenoxyethanol, Cetearyl Alcohol, Chlorphenesin, Disodium EDTA, Aluminum Hydroxide, Iron Oxides

Questions?

866-428-3366; Outside US, dial collect 215-273-8755 www.aveeno.com

Distributed by:
Kenvue Brands LLC
Summit, NJ 07901

PRINCIPAL DISPLAY PANEL - 48mL Carton Label

NEW

Aveeno®

Calm +

Restore

DAILY

MOISTURIZER

mineral sunscreen

BROAD SPECTURM

SPF 30

ZINC OXIDE

TITANIUM DIOXIDE

Sensitive Skin

Lightweight

all day moisture

FRAGRANCE FREE

SPF

30

DERMATOLOGIST RECOMMENDED BRAND

SOOTHING OAT+ FEVERFEW

1.7 FL OZ (48 mL)